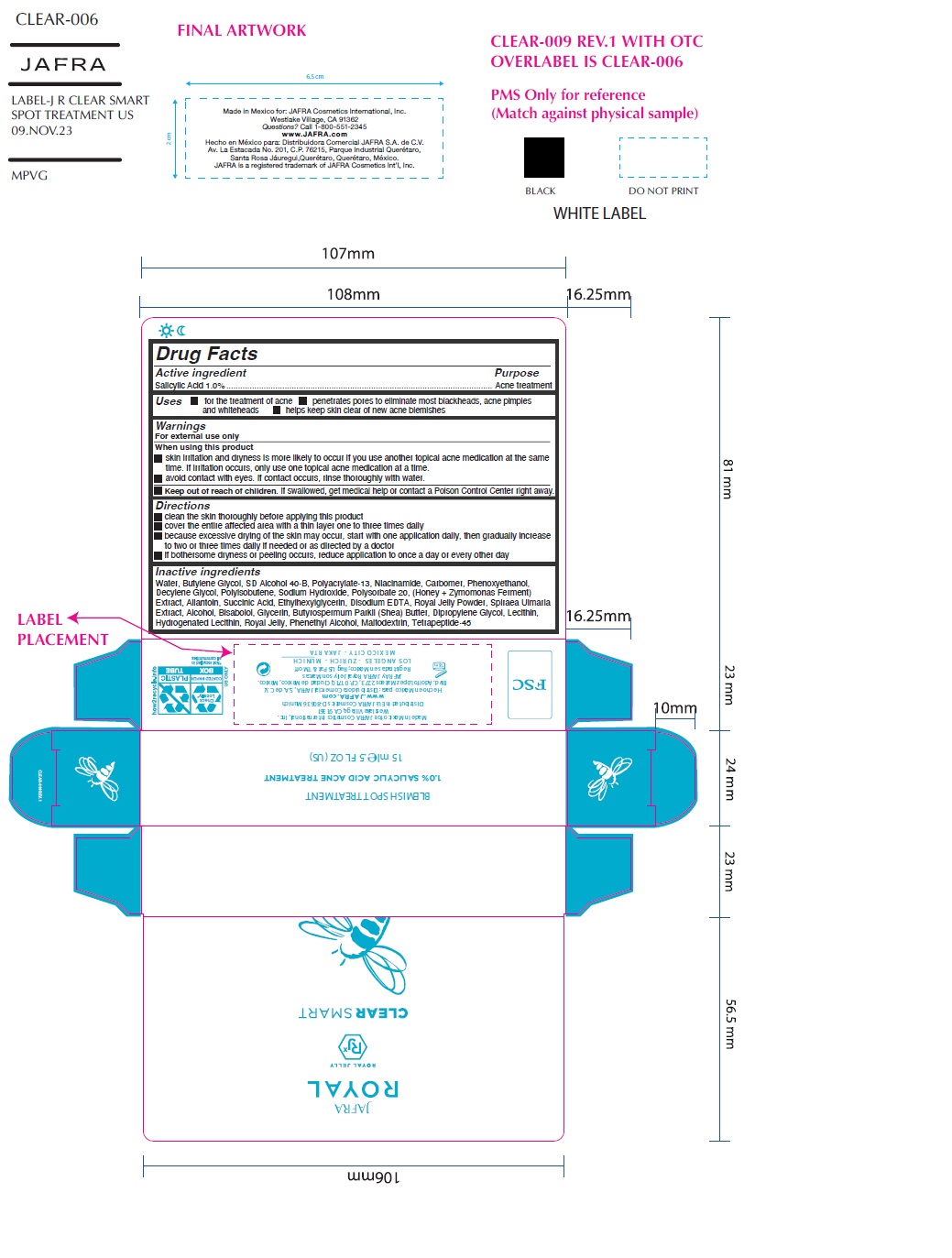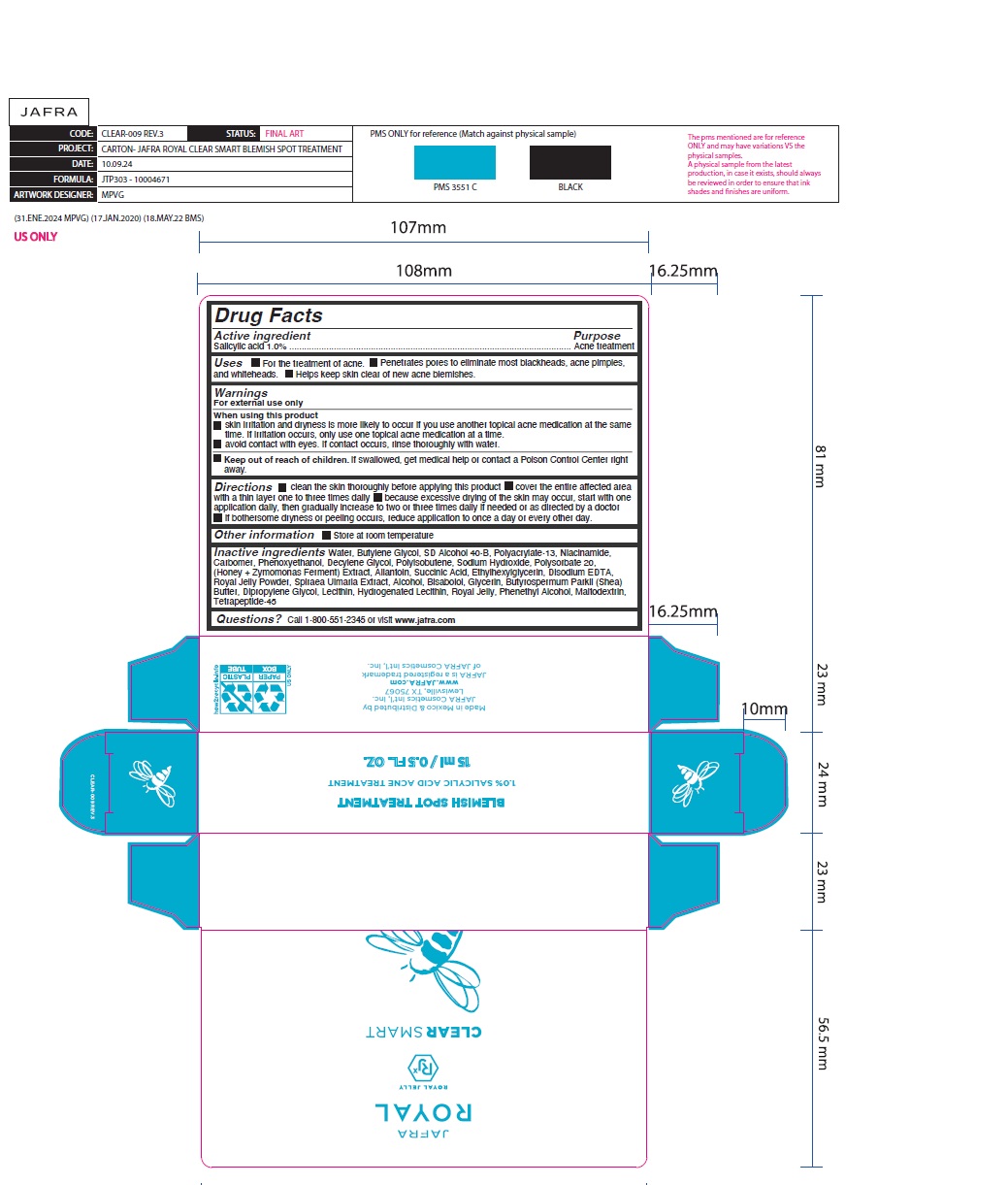 DRUG LABEL: Clear Smart Blemish Spot Treatment
NDC: 68828-245 | Form: GEL
Manufacturer: Distribuidora Comercial Jafra, S.A. de C.V
Category: otc | Type: HUMAN OTC DRUG LABEL
Date: 20251021

ACTIVE INGREDIENTS: SALICYLIC ACID 1 g/100 mL
INACTIVE INGREDIENTS: SODIUM HYDROXIDE; WATER; SHEA BUTTER; ETHYLHEXYLGLYCERIN; GLYCERIN; ALLANTOIN; NIACINAMIDE; LEVOMENOL; BUTYLENE GLYCOL; HONEY; HYDROGENATED SOYBEAN LECITHIN; MALTODEXTRIN; LECITHIN, SOYBEAN; PHENYLETHYL ALCOHOL; CARBOMER HOMOPOLYMER, UNSPECIFIED TYPE; DECYLENE GLYCOL; DIPROPYLENE GLYCOL; EDETATE DISODIUM; PHENOXYETHANOL; ROYAL JELLY; ALCOHOL; SUCCINIC ACID; POLYACRYLATE-13; POLYISOBUTYLENE (1300 MW); POLYSORBATE 20; FILIPENDULA ULMARIA ROOT

Clear Smart Blemish Spot Treatment

Active ingredient

Salicylic Acid 1%

Purpose

Acne treatment

Uses

- For the treatment of acne.
- Penetrates pores to eliminate most blackheads, acne pimples, and whiteheads.
- Helps keep skin clear of new acne blemishes.

Warnings

For external use only

When using this product

- skin irritation and dryness is more likely to occur if you use another topical acne medication at the same time. If irritation occurs, only use one topical acne medication at a time.
- avoid contact with eyes. If contact occurs, rinse thoroughly with water.

Keep out of reach of children.If swallowed, get medical help or contact a Poison Control Center right away.

Directions

- Clean the skin thoroughly before applying this product
- Cover the entire affected area with a thin layer one to three times daily
- Because excessive drying of the skin may occur, start with one application daily, then gradually increase to two or three times daily if needed or as directed by a doctor
- If bothersome dryness or peeling occurs, reduce application to once a day or every other day.

Other information

- Store at room temperature

Inactive ingredients

Water, Butylene Glycol, SD Alcohol 40-B, Polyacrylate-13, Niacinamide, Carbomer, Phenoxyethanol, Decylene Glycol, Polyisobutene, Sodium Hydroxide, Polysorbate 20, (Honey + Zymomonas Ferment) Extract, Allantoin, Succinic Acid, Ethylhexylglycerin, Disodium EDTA, Royal Jelly Powder, Spiraea Ulmaria Extract, Alcohol, Bisabolol, Glycerin, Butyrospermum Parkii (Shea) Butter, Dipropylene Glycol, Lecithin, Hydrogenated Lecithin, Royal Jelly, Phenethyl Alcohol, Maltodextrin, Tetrapeptide-45

Questions?Call 1-800-551-2345 or visit www.jafra.com